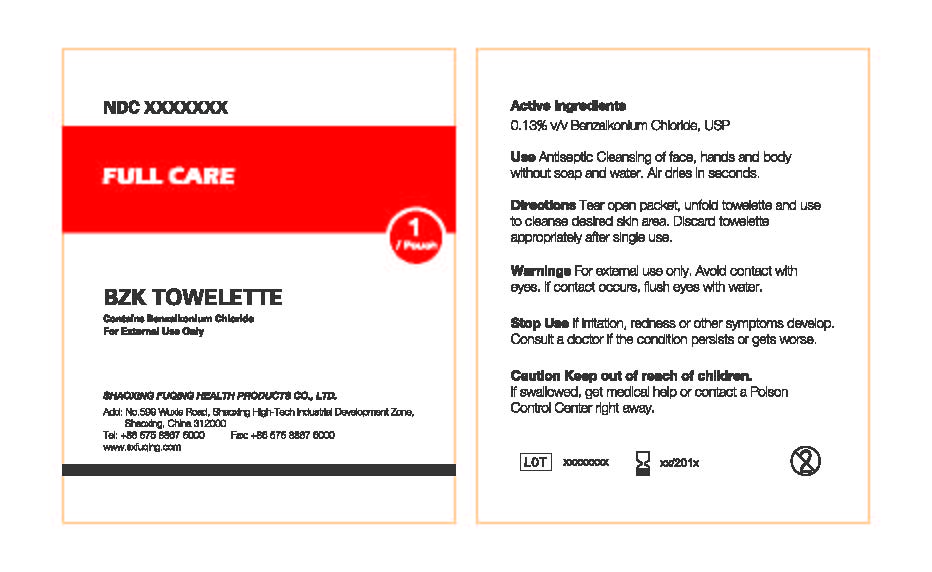 DRUG LABEL: Full Care  BZK Towelette
NDC: 65028-002 | Form: SOLUTION
Manufacturer: Shaoxing Fuqing Health Products Co., Ltd.
Category: otc | Type: HUMAN OTC DRUG LABEL
Date: 20140606

ACTIVE INGREDIENTS: BENZALKONIUM CHLORIDE 0.0026 g/2 mL
INACTIVE INGREDIENTS: WATER

Active Ingredient: Benzalkonium Chloride (0.13%)

Purpose: Antiseptic

INDICATIONS AND USAGE

Use: Antiseptic cleasing of face, hands, and body without soap and water. Air dries in seconds.

Warnings:

For external use only

Avoid contact with eyes. If contact occurs, flush eyes with water.

Keep out of reach of children. If swallowed, get medical help or consult a poison control center right away

Stop use if irritation, redness, or other syptoms develop.

Consult a doctor if condition persists or gets worse.

Directions:

Tear open packet, unfold towelette and use to cleanse desired skin area. Discard toweletted appropriately after single use.

Inactive Ingredient

Purified water